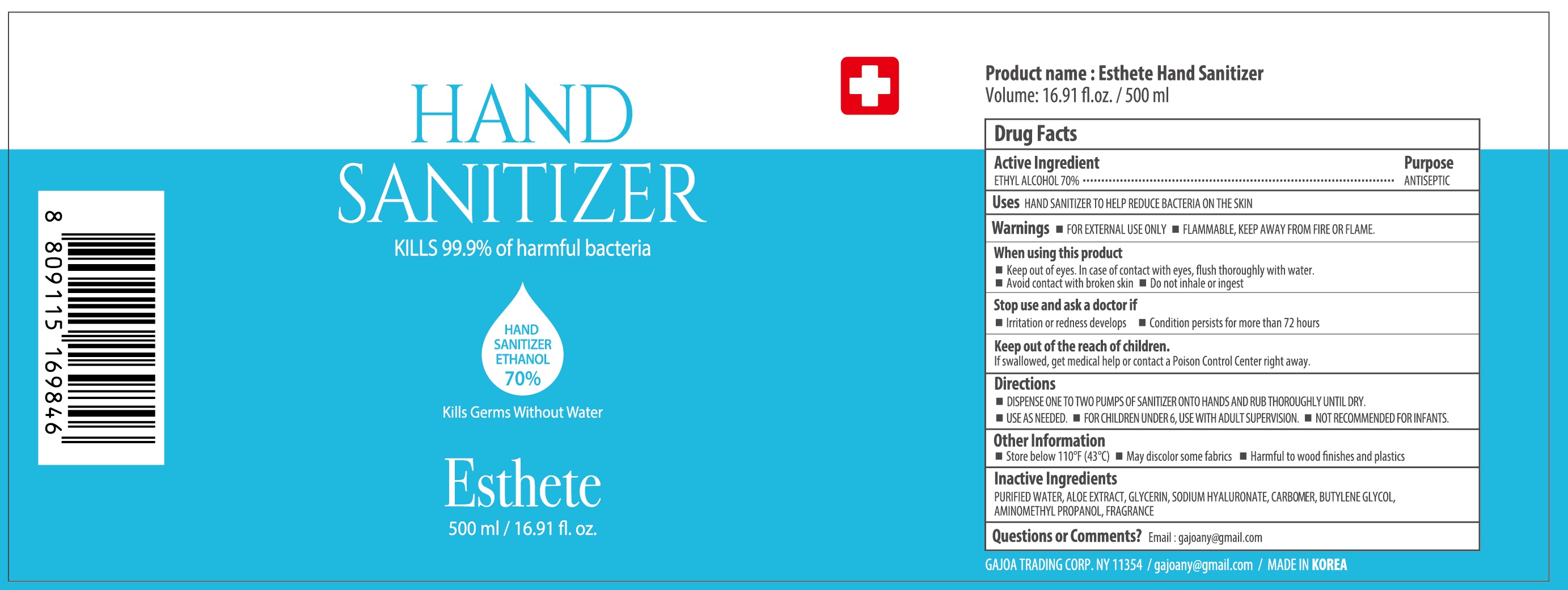 DRUG LABEL: ESTHETE HAND SANITIZER
NDC: 55526-0014 | Form: GEL
Manufacturer: EQMAXON Corp
Category: otc | Type: HUMAN OTC DRUG LABEL
Date: 20200530

ACTIVE INGREDIENTS: ALCOHOL 350 mL/500 mL
INACTIVE INGREDIENTS: Water; ALOE; Glycerin; HYALURONATE SODIUM; CARBOMER HOMOPOLYMER, UNSPECIFIED TYPE; Butylene Glycol; AMINOMETHYLPROPANOL

ACTIVE INGREDIENT

Ethyl Alcohol 70.0%

INACTIVE INGREDIENTS

PURIFIED WATER, ALOE EXTRACT, GLYCERIN, SODIUM HYALURONATE, CARBOMER, BUTYLENE GLYCOL, AMINOMETHYL PROPANOL, FRAGRANCE

PURPOSE

ANTISEPTIC

WARNINGS

▪ FOR EXTERNAL USE ONLY ▪ FLAMMABLE, KEEP AWAY FROM FIRE AND FLAME

When using this product
▪Keep out of eyes. In case of contact with eyes, flush thoroughly with water. ▪ Avoid contact with broken skin ▪ Do not inhale or ingest.

Stop use and ask a doctor if irritation or redness develops.

KEEP OUT OF REACH OF CHILDREN

If swallowed, get medical help or contact a Poison Control Center right away

Uses

HAND SANITIZER TO HELP REDUCE BACTERIA ON THE SKIN

Directions

▪ DISPENSE ONE TO TWO PUMPS OF SANITIZER ONTO HANDS AND RUB THOROUGHLY UNTIL DRY.

▪ USE AS NEEDED ▪ FOR CHILDREN UNDER 6, USE WITH ADULT SUPERVISION

▪ NOT RECOMMENDED FOR INFANTS

Other Information

▪ Store below 110 °F(43°C)

▪ May discolor some fabrics

▪ Harmful to wood finishes and plastics

Questions or Comments?

Email : gajoany@gmail.com